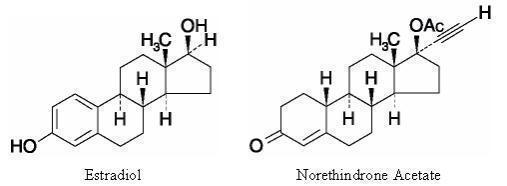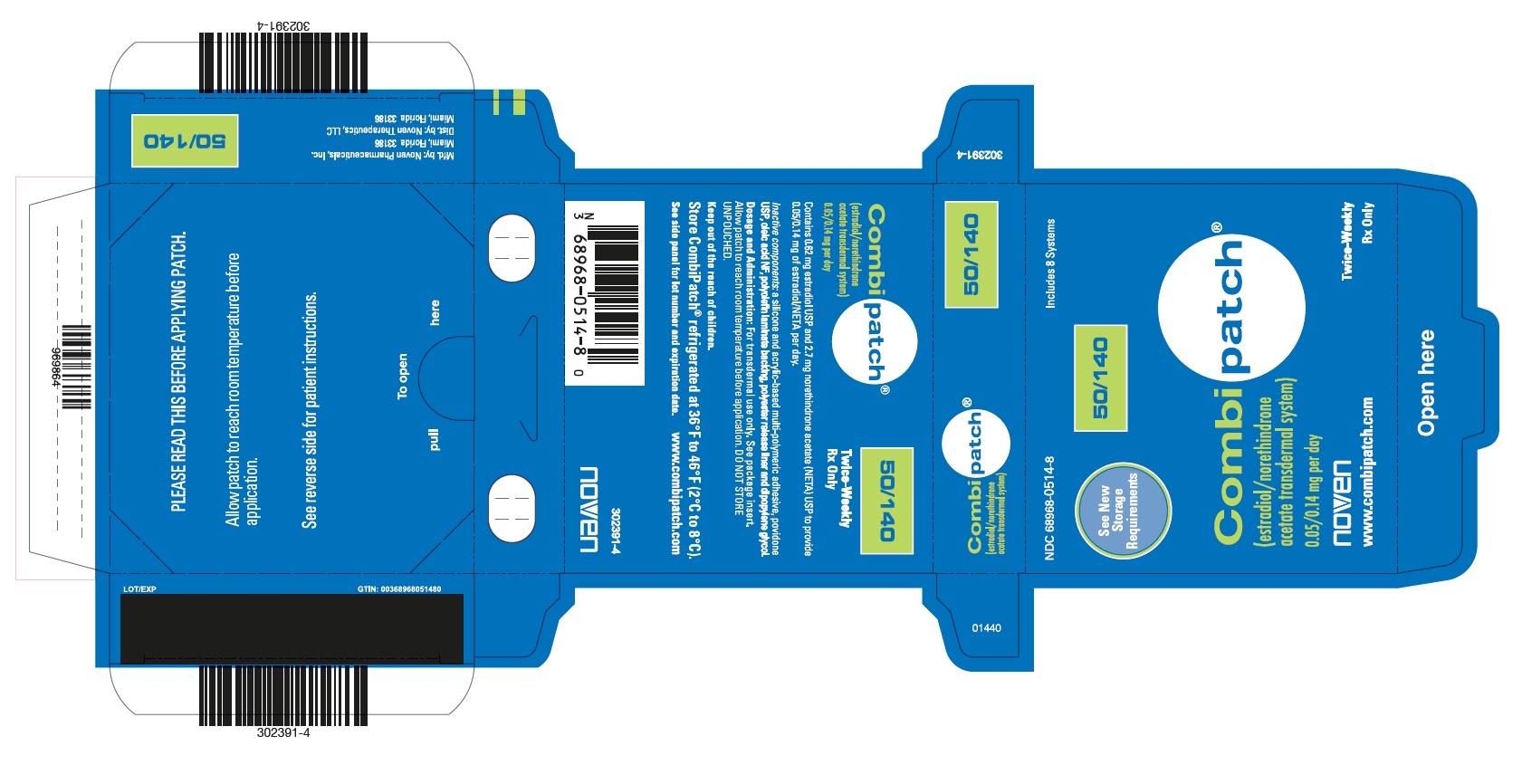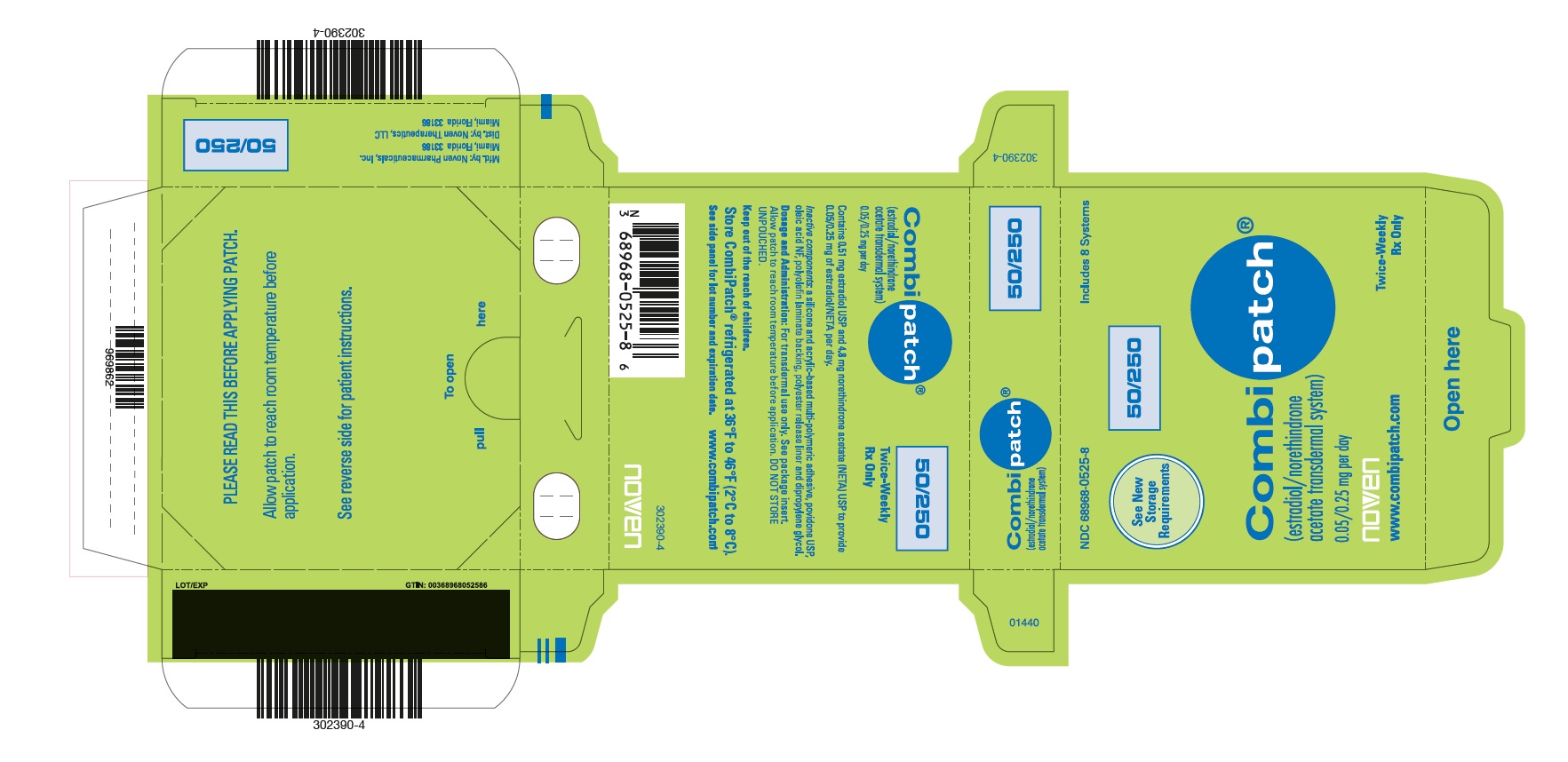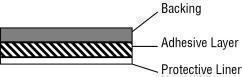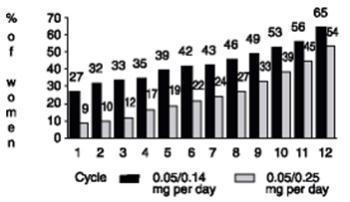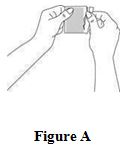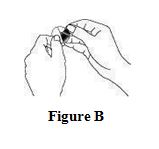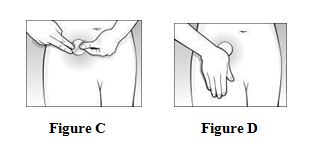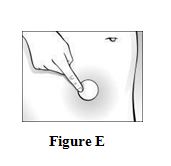 DRUG LABEL: CombiPatch (estradiol/norethindrone acetate transdermal system)
NDC: 68968-0514 | Form: PATCH, EXTENDED RELEASE
Manufacturer: Noven Therapeutics, LLC
Category: prescription | Type: HUMAN PRESCRIPTION DRUG LABEL
Date: 20240221

ACTIVE INGREDIENTS: ESTRADIOL 0.05 mg/1 d; NORETHINDRONE ACETATE 0.14 mg/1 d
INACTIVE INGREDIENTS: DIPROPYLENE GLYCOL; OLEIC ACID; POVIDONE K30

CombiPatch®
(estradiol/norethindrone acetate transdermal system)
Rx only
Prescribing Information

WARNING:
CARDIOVASCULAR DISORDERS, BREAST CANCER, ENDOMETRIAL CANCER, AND PROBABLE DEMENTIA

Estrogen Plus Progestin Therapy

Cardiovascular Disorders and Probable Dementia

Estrogen plus progestin therapy should not be used for the prevention of cardiovascular disease or dementia. (See CLINICAL STUDIES and WARNINGS, Cardiovascular Disorders and Probable Dementia).

The Women’s Health Initiative (WHI) estrogen plus progestin substudy reported an increased risk of deep vein thrombosis (DVT), pulmonary embolism (PE), stroke and myocardial infarction (MI) in postmenopausal women (50 to 79 years of age) during 5.6 years of treatment with daily oral conjugated estrogens (CE) [0.625 mg] combined with medroxyprogesterone acetate (MPA) [2.5 mg], relative to placebo. (See CLINICAL STUDIES and WARNINGS, Cardiovascular Disorders).

The WHI Memory Study (WHIMS) estrogen plus progestin ancillary study of the WHI reported an increased risk of developing probable dementia in postmenopausal women 65 years of age or older during 4 years of treatment with daily CE (0.625 mg) combined with MPA (2.5 mg), relative to placebo. It is unknown whether this finding applies to younger postmenopausal women. (See CLINICAL STUDIES and WARNINGS, Probable Dementia and PRECAUTIONS, Geriatric Use).

Breast Cancer

The WHI estrogen plus progestin substudy demonstrated an increased risk of invasive breast cancer. (See CLINICAL STUDIES and WARNINGS, Malignant Neoplasms, Breast Cancer).

In the absence of comparable data, these risks should be assumed to be similar for other doses of CE and MPA, and other combinations and dosage forms of estrogens and progestins. Estrogens with or without progestins should be prescribed at the lowest effective doses and for the shortest duration consistent with treatment goals and risks for the individual woman.

Estrogen-Alone Therapy

Endometrial Cancer

There is an increased risk of endometrial cancer in a woman with a uterus who uses unopposed estrogens. Adding a progestin to estrogen therapy has been shown to reduce the risk of endometrial hyperplasia, which may be a precursor to endometrial cancer. Adequate diagnostic measures, including directed or random endometrial sampling when indicated, should be undertaken to rule out malignancy in postmenopausal women with undiagnosed persistent or recurring abnormal genital bleeding. (See WARNINGS, Malignant Neoplasms, Endometrial Cancer).

Cardiovascular Disorders and Probable Dementia

Estrogen-alone therapy should not be used for the prevention of cardiovascular disease or dementia (See CLINICAL STUDIES and WARNINGS, Cardiovascular Disorders and Probable Dementia).

The WHI estrogen-alone substudy reported increased risks of stroke and DVT in postmenopausal women (50 to 79 years of age) during 7.1 years of treatment with daily oral CE (0.625 mg)-alone, relative to placebo. (See CLINICAL STUDIES and WARNINGS, Cardiovascular Disorders).

The WHIMS estrogen-alone ancillary study of the WHI reported an increased risk of developing probable dementia in postmenopausal women 65 years of age or older during 5.2 years of treatment with daily CE (0.625 mg)-alone, relative to placebo. It is unknown whether this finding applies to younger postmenopausal women. (See CLINICAL STUDIES and WARNINGS, Probable Dementia and PRECAUTIONS, Geriatric Use).

In the absence of comparable data, these risks should be assumed to be similar for other doses of CE and other dosage forms of estrogens. Estrogens with or without progestins should be prescribed at the lowest effective doses and for the shortest duration consistent with treatment goals and risks for the individual woman.

DESCRIPTION

CombiPatch® (estradiol/norethindrone acetate transdermal system) is an adhesive-based matrix transdermal patch designed to release both estradiol, an estrogen, and norethindrone acetate (NETA), a progestational agent, continuously upon application to intact skin.

Two systems are available, providing the following in vivo delivery rates of estradiol and NETA.

System Size | Estradiol (mg) | NETA ^1 (mg) | Nominal Delivery Rate ^2 (mg per day) Estradiol / NETA
9 cm ^2 round | 0.62 | 2.7 | 0.05/0.14
16 cm ^2 round | 0.51 | 4.8 | 0.05/0.25
^1NETA=norethindrone acetate.
^2Based on in vivo/in vitro flux data, delivery of both components per day via skin of average permeability (interindividual variation in skin permeability is approximately 20 percent).

Estradiol USP (estradiol) is a white to creamy white, odorless, crystalline powder, chemically described as estra-1,3,5(10)-triene-3,17 β-diol. The molecular weight of estradiol is 272.39 and the molecular formula is C18H24O2.

NETA USP is a white to creamy white, odorless, crystalline powder, chemically described as 17-hydroxy-19-nor-17α-pregn-4-en-20-yn-3-one acetate. The molecular weight of NETA is 340.47 and the molecular formula is C22H28O3.

The structural formulas for estradiol and NETA are:

CombiPatch is comprised of 3 layers. Proceeding from the visible surface toward the surface attached to the skin, these layers are (1) a translucent polyolefin film backing, (2) an adhesive layer containing estradiol, NETA, acrylic adhesive, silicone adhesive, oleic acid NF, povidone USP and dipropylene glycol, and (3) a polyester release protective liner, which is attached to the adhesive surface and must be removed before the system can be used.

The active components of the system are estradiol USP and NETA USP. The remaining components of the system are pharmacologically inactive.

CLINICAL PHARMACOLOGY

Endogenous estrogens are largely responsible for the development and maintenance of the female reproductive system and secondary sexual characteristics. Although circulating estrogens exist in a dynamic equilibrium of metabolic interconversions, estradiol is the principal intracellular human estrogen and is substantially more potent than its metabolites, estrone and estriol at the receptor level.

The primary source of estrogen in normally cycling adult women is the ovarian follicle, which secretes 70 to 500 mcg of estradiol daily, depending on the phase of the menstrual cycle. After menopause, most endogenous estrogen is produced by conversion of androstenedione, secreted by the adrenal cortex, to estrone in the peripheral tissues. Thus, estrone and the sulfate conjugated form, estrone sulfate, are the most abundant circulating estrogens in postmenopausal women.

Estrogens act through binding to nuclear receptors in estrogen-responsive tissues. To date, 2 estrogen receptors have been identified. These vary in proportion from tissue to tissue.

Circulating estrogens modulate the pituitary secretion of the gonadotropins, luteinizing hormone (LH), and follicle stimulating hormone (FSH) through a negative feedback mechanism. Estrogens act to reduce the elevated levels of these hormones seen in postmenopausal women.

Pharmacokinetics

Absorption

Estradiol: Estrogens used in hormone therapy are well absorbed through the skin, mucous membranes, and gastrointestinal tract. Administration of CombiPatch every 3 to 4 days in postmenopausal women produces average steady-state estradiol serum concentrations of 45 to 50 pg/mL, which are equivalent to the normal ranges observed at the early follicular phase in premenopausal women. These concentrations are achieved within 12 to 24 hours following CombiPatch application. Minimal fluctuations in serum estradiol concentrations are observed following CombiPatch application, indicating consistent hormone delivery over the application interval.

In 1 study, serum concentrations of estradiol were measured in 40 healthy, postmenopausal women throughout 3 consecutive CombiPatch applications to the abdomen (each dose was applied for three 3.5-day periods). The corresponding pharmacokinetic parameters are summarized in Table 1.

Table 1. Mean (SD) Serum Estradiol and Estrone Concentrations (pg/mL) at Steady-State (Uncorrected for Baseline Levels)
Estradiol
System Size | Dose Estradiol/NETA (mg per day) | C max | C min | C avg
9 cm ^2 | 0.05/0.14 | 71 (32) | 27 (17) | 45 (21)
16 cm ^2 | 0.05/0.25 | 71 (30) | 37 (17) | 50 (21)
Estrone
9 cm ^2 | 0.05/0.14 | 72 (23) | 49 (19) | 54 (19)
16 cm ^2 | 0.05/0.25 | 78 (22) | 58 (22) | 60 (18)

Norethindrone: Progestins used in hormone therapy are well absorbed through the skin, mucous membranes, and gastrointestinal tract. Norethindrone steady-state concentrations are attained within 24 hours of application of the CombiPatch transdermal delivery systems. Minimal fluctuations in serum norethindrone concentrations are observed following CombiPatch treatment, indicating consistent hormone delivery over the application interval. Serum concentrations of norethindrone increase linearly with increasing doses of NETA.

In 1 study, serum concentrations of norethindrone were measured in 40 healthy, postmenopausal women throughout 3 consecutive CombiPatch applications to the abdomen (each dose was applied for three 3.5-day periods). The corresponding pharmacokinetic parameters are summarized in Table 2.

Table 2. Mean (SD) Serum Norethindrone Concentrations (pg/mL) at Steady-State
System Size | Dose Estradiol/NETA (mg per day) | C max | C min | C avg
9 cm ^2 | 0.05/0.14 | 617 (341) | 386 (137) | 489 (244)
16 cm ^2 | 0.05/0.25 | 1060 (543) | 686 (306) | 840 (414)

Distribution

Estradiol: The distribution of exogenous estrogens is similar to that of endogenous estrogens. Estrogens are widely distributed in the body and are generally found in higher concentrations in the sex hormone target organs. Estrogens circulate in the blood largely bound to sex hormone-binding globulin (SHBG) and albumin.

Norethindrone: In plasma, norethindrone is bound approximately 90 percent to SHBG and albumin.

Metabolism

Estradiol: Exogenous estrogens are metabolized in the same manner as endogenous estrogens. Circulating estrogens exist in a dynamic equilibrium of metabolic interconversions. These transformations take place mainly in the liver. Estradiol is converted reversibly to estrone, and both can be converted to estriol, which is a major urinary metabolite. Estrogens also undergo enterohepatic recirculation via sulfate and glucuronide conjugation in the liver, biliary secretion of conjugates into the intestine, and hydrolysis in the intestine followed by reabsorption. In postmenopausal women a significant portion of the circulating estrogens exist as sulfate conjugates, especially estrone sulfate, which serves as a circulating reservoir for the formation of more active estrogens.

Norethindrone: NETA is hydrolyzed to the active moiety, norethindrone, in most tissues including skin and blood. Norethindrone is primarily metabolized in the liver.

Excretion

Estradiol: Estradiol, estrone, and estriol are excreted in the urine along with glucuronide and sulfate conjugates. Estradiol has a short elimination half-life of approximately 2 to 3 hours; therefore, a rapid decline in serum levels is observed after the CombiPatch estradiol/NETA transdermal system is removed. Within 4 to 8 hours serum estradiol concentrations return to untreated, postmenopausal levels (less than 20 pg/mL).

Concentration data from clinical trials indicate that the pharmacokinetics of estradiol did not change over time, suggesting no evidence of the accumulation of estradiol following extended patch wear periods (up to 1 year).

Norethindrone: The elimination half-life of norethindrone is reported to be 6 to 8 hours. Norethindrone serum concentrations diminish rapidly and are less than 50 pg/mL within 48 hours after removal of the CombiPatch transdermal delivery system.

Concentration data from clinical trials indicate that the pharmacokinetics of norethindrone did not change over time, suggesting no evidence of the accumulation of norethindrone following extended patch wear periods (up to 1 year).

Special Populations

No pharmacokinetic studies were conducted in special populations, including patients with renal or hepatic impairment.

Drug Interactions

No drug interaction studies have been conducted with CombiPatch. In vitro and in vivo studies have shown that estrogens are metabolized partially by cytochrome P450 3A4 (CYP3A4). Therefore, inducers or inhibitors of CYP3A4 may affect estrogen drug metabolism. Inducers of CYP3A4 such as St. John’s wort (Hypericum perforatum) preparations, anticonvulsants (e.g., phenobarbital, phenytoin and carbamazepine), phenylbutazone, and anti-infectives (e.g., rifampin, rifabutin, nevirapine and efavirenz) may reduce plasma concentrations of estrogens, possibly resulting in a decrease in therapeutic effects and/or changes in the uterine bleeding profile. Inhibitors of CYP3A4 such as erythromycin, clarithromycin, ketoconazole, itraconazole, ritonavir, nelfinavir and grapefruit juice may increase plasma concentrations of estrogens and may result in side effects.

Adhesion

Averaging across 6 clinical trials lasting 3 months to 1 year, of 1,287 patients treated, CombiPatch transdermal systems completely adhered to the skin nearly 90 percent of the time over the 3- to 4-day wear period. Less than 2 percent of the patients required reapplication or replacement of systems due to lifting or detachment. Two patients (0.2 percent) discontinued therapy during clinical trials due to adhesion failure.

CLINICAL STUDIES

Effects on Vasomotor Symptoms

In 2 clinical trials designed to assess the degree of relief of moderate to severe vasomotor symptoms in postmenopausal women (n=332), CombiPatch was administered for 3 28-day cycles in Continuous Combined or Continuous Sequential treatment regimens versus placebo. In the Continuous Combined regimen, CombiPatch was applied throughout the 3 cycles, replacing the system twice weekly. In the Continuous Sequential regimen, an estradiol-only transdermal system (Vivelle® 0.05 mg) was applied twice weekly during the first 14 days of a 28-day cycle; CombiPatch was applied for the remaining 14 days of the cycle and replaced twice weekly, as well. The mean number of hot flushes at baseline were 10 to 11 per day and 11 to 12 per day in the Continuous Combined and Continuous Sequential regimen trials, respectively. The mean number and intensity of daily hot flushes (intent-to-treat population) was significantly reduced from baseline to endpoint with either the Continuous Combined or Continuous Sequential administration of CombiPatch at all doses as compared to placebo (intent-to-treat population). (See Tables 3 and 4)

Table 3. Adjusted Mean Change in the Number of Hot Flushes and Daily Intensity of Hot Flushes per Day in CombiPatch Continuous Combined Transdermal Therapy
 | CombiPatch Continuous Combined |  | Placebo
Adjusted Mean Change from Baseline^1 | 0.05/0.14 mg per day^2 n=57 | 0.05/0.25 mg per day^2 n=52 | n=51
Number of Hot Flushes^3 | -9.3^5 | -8.9^5 | -6.2
Daily Intensity of Hot Flushes^3,4 | -4.6^5,6 | -5.0^5 | -2.8^7
^1Means were adjusted for imbalance among treatment groups and investigators (least squares mean from ANOVA).
^2Represents the milligrams of estradiol/NETA delivered daily by each system.
^3Population represents those patients who had baseline and endpoint observations.
^4The intensity of hot flushes was evaluated on a scale of 0 to 9 (none=0, mild=1-3, moderate= 4-6, severe=7-9).
^5P-value versus placebo = <0.001.
^6Total number of patients with available data is 56.
^7Total number of patients with available data is 50.

Table 4. Adjusted Mean Change in the Number of Hot Flushes and Daily Intensity of Hot Flushes per Day in CombiPatch Continuous Sequential Transdermal Therapy
 | CombiPatch® Continuous Combined |  | Placebo
Adjusted Mean Change from Baseline^1 | 0.05/0.14 mg per day^2 n=54 | 0.05/0.25 mg per day^2 n=59 | n=53
Number of Hot Flushes^3 | -9.3^5 | -9.5^5 | -5.5
Daily Intensity of Hot Flushes^3,4 | -4.4^5 | -4.5^5 | -2.1
^1Means were adjusted for imbalance among treatment groups and investigators (least squares mean from ANOVA).
^2Represents the milligrams of estradiol/NETA delivered daily by each system.
^3Population represents those patients who had baseline and endpoint observations.
^4The intensity of hot flushes was evaluated on a scale of 0 to 9 (none=0, mild=1-3, moderate= 4-6, severe=7-9).
^5P-value versus placebo = <0.001.

Effects on the Endometrium

The use of unopposed estrogen therapy has been associated with an increased risk of endometrial hyperplasia, a possible precursor of endometrial adenocarcinoma. Progestins counter the estrogenic effects by decreasing the number of nuclear estradiol receptors and suppressing epithelial DNA synthesis in endometrial tissue.

Clinical studies indicate that the addition of a progestin to an estrogen regimen at least 12 days per cycle reduces the incidence of endometrial hyperplasia and the potential risk of adenocarcinoma in women with intact uteri. The addition of a progestin to an estrogen regimen has not been shown to interfere with the efficacy of estrogen therapy for its approved indications.

CombiPatch was effective in reducing the incidence of estrogen-induced endometrial hyperplasia after 1 year of therapy in two clinical trials. Nine hundred fifty-five (955) postmenopausal women (with intact uteri) were treated with (i) a continuous regimen of CombiPatch alone (Continuous Combined regimen), (ii) a sequential regimen with an estradiol-only (Vivelle 0.05 mg) transdermal system followed by a CombiPatch transdermal system (Continuous Sequential regimen), or (iii) continuous regimen with an estradiol-only transdermal system (Vivelle 0.05 mg). The incidence of endometrial hyperplasia (primary endpoint) was significantly less after 1 year of therapy with either CombiPatch regimen than with the estradiol-only transdermal system. Tables 5 and 6 summarize these results (intent-to-treat populations).

Table 5. Incidence of Endometrial Hyperplasia in a Continuous Combined CombiPatch Regimen
 | CombiPatch Continuous Combined |  | Vivelle Continuous
 | 0.05/0.14 mg per day^1 | 0.05/0.25 mg per day^1 | 0.05 mg per day
Number of Patients with Biopsies^2 | 123 | 98 | 103
Number (%) of Patients with Hyperplasia | 1 (<1%)^3 | 1 (1%)^3,4 | 39 (38%)^5
^1Represents milligrams of estradiol/NETA delivered daily by each system.
^2Biopsy after 12 cycles of treatment or hyperplasia before cycle 12.
^3Comparison of continuous combined regimen versus estradiol-only patch was significant (p <0.001).
^4This patient had hyperplasia at baseline.
^5One of 39 patients had hyperplasia in an endometrial polyp.

Table 6. Incidence of Endometrial Hyperplasia in a Continuous Sequential CombiPatch Regimen
 | CombiPatch Continuous Sequential |  | Vivelle Continuous
 | 0.05/0.14 mg per day^1 | 0.05/0.25 mg per day^1 | 0.05 mg per day
Number of Patients with Biopsies^2 | 117 | 114 | 115
Number (%) of Patients with Hyperplasia | 1 (<1%)^3,4 | 1 (<1%)^3,5 | 23 (20%)
^1Represents milligrams of estradiol/NETA delivered daily by each system.
^2Biopsy after 12 cycles of treatment or hyperplasia before cycle 12.
^3Comparison of continuous sequential regimen versus estradiol-only patch was significant (p <0.001).
^4This patient had hyperplasia at baseline.
^5This patient had hyperplasia in an endometrial polyp.

Effects on Uterine Bleeding or Spotting

With the Continuous Combined regimen, of the women treated with CombiPatch and who completed the 1-year study, the incidence of cumulative amenorrhea (the absence of bleeding or spotting during a 28-day cycle and sustained to the end of the study) increased over time. The incidence of amenorrhea from cycle 10 through 12 was 53 percent and 39 percent for the CombiPatch 0.05/0.14 mg per day and CombiPatch 0.05/0.25 mg per day treatment groups, respectively. Women who experienced bleeding usually characterized it as light (intensity of 1.3 on a scale of 1 to 4) with a duration of 4 and 6 days for the CombiPatch 0.05/0.14 mg per day and CombiPatch 0.05/0.25 mg per day treatment groups, respectively. (See Figure 1)

Figure 1. Incidence of Cumulative Amenorrhea* in CombiPatch Continuous Combined Transdermal Therapy by Cycle Over a 1-Year Period (Intent-to-Treat Population)

*Cumulative amenorrhea is defined as the absence of bleeding for the duration of a 28-day cycle and sustained to the end of the study.

Women’s Health Initiative Studies

The WHI enrolled approximately 27,000 predominantly healthy postmenopausal women in two substudies to assess the risks and benefits of daily oral CE (0.625 mg)-alone or in combination with MPA (2.5 mg) compared to placebo in the prevention of certain chronic diseases. The primary endpoint was the incidence of coronary heart disease (CHD) [defined as nonfatal MI, silent MI and CHD death], with invasive breast cancer as the primary adverse outcome. A “global index” included the earliest occurrence of CHD, invasive breast cancer, stroke, PE, endometrial cancer (only in the CE plus MPA substudy), colorectal cancer, hip fracture, or death due to other cause. These substudies did not evaluate the effects of CE plus MPA or CE-alone on menopausal symptoms.

WHI Estrogen Plus Progestin Substudy

The WHI estrogen plus progestin substudy was stopped early. According to the predefined stopping rule, after an average follow-up of 5.6 years of treatment, the increased risk of invasive breast cancer and cardiovascular events exceeded the specified benefits included in the “global index.” The absolute excess risk of events included in the “global index” was 19 per 10,000 women-years.

For those outcomes included in the WHI “global index” that reached statistical significance after 5.6 years of follow-up, the absolute excess risks per 10,000 women years in the group treated with CE plus MPA were 7 more CHD events, 8 more strokes, 10 more PEs, and 8 more invasive breast cancers, while the absolute risk reductions per 10,000 women-years were 6 fewer colorectal cancers and 5 fewer hip fractures.

Results of the estrogen plus progestin substudy, which included 16,608 women (average 63 years of age, range 50 to 79 years; 83.9 percent white, 6.8 percent black, 5.4 percent Hispanic, 3.9 percent Other), are presented in Table 7. These results reflect centrally adjudicated data after an average follow-up of 5.6 years.

Table 7. Relative and Absolute Risk Seen in the Estrogen Plus Progestin Substudy of WHI at an Average of 5.6 Yearsa,b
Event | Relative Risk CE/MPA vs. Placebo (95% nCIc) | CE/MPA n=8,506 | Placebo n=8,102
 |  | Absolute Risk per 10,000 Women-Years
CHD events | 1.23 (0.99–1.53) | 41 | 34
Nonfatal MI | 1.28 (1.00–1.63) | 31 | 25
CHD death | 1.10 (0.70–1.75) | 8 | 8
All strokes | 1.31 (1.03–1.68) | 33 | 25
Ischemic stroke | 1.44 (1.09–1.90) | 26 | 18
Deep vein thrombosisd | 1.95 (1.43–2.67) | 26 | 13
Pulmonary embolism | 2.13 (1.45–3.11) | 18 | 8
Invasive breast cancere | 1.24 (1.01–1.54) | 41 | 33
Colorectal cancer | 0.61 (0.42–0.87) | 10 | 16
Endometrial cancerd | 0.81 (0.48–1.36) | 6 | 7
Cervical cancerd | 1.44 (0.47–4.42) | 2 | 1
Hip fracture | 0.67 (0.47–0.96) | 11 | 16
Vertebral fracturesd | 0.65 (0.46–0.92) | 11 | 17
Lower arm/wrist fracturesd | 0.71 (0.59–0.85) | 44 | 62
Total fracturesd | 0.76 (0.69–0.83) | 152 | 199
Overall mortalityf | 1.00 (0.83–1.19) | 52 | 52
Global Indexg | 1.13 (1.02–1.25) | 184 | 165
aAdapted from numerous WHI publications. WHI publications can be viewed at www.nhlbi.nih.gov/whi.
bResults are based on centrally adjudicated data.
cNominal confidence intervals (CI) unadjusted for multiple looks and multiple comparisons.
dNot included in “global index”.
eIncludes metastatic and non-metastatic breast cancer, with the exception of in situ breast cancer.
fAll deaths, except from breast or colorectal cancer, definite or probable CHD, PE or cerebrovascular disease.
gA subset of the events was combined in a “global index”, defined as the earliest occurrence of CHD events, invasive breast cancer, stroke, pulmonary embolism, colorectal cancer, hip fracture, or death due to other causes.

Timing of the initiation of estrogen plus progestin therapy relative to the start of menopause may affect the overall risk benefit profile. The WHI estrogen plus progestin substudy stratified by age showed in women 50 to 59 years of age a nonsignificant trend toward reduced risk for overall mortality [hazard ratio (HR) 0.69 (95 percent CI 0.44 to 1.07)].

WHI Estrogen-Alone Substudy

The WHI estrogen-alone substudy was stopped early because an increased risk of stroke was observed, and it was deemed that no further information would be obtained regarding the risks and benefits of estrogen-alone in predetermined primary endpoints.

Results of the estrogen-alone substudy, which included 10,739 women (average 63 years of age, range 50 to 79 years; 75.3 percent white, 15.1 percent black, 6.1 percent Hispanic, 3.6 percent Other) after an average follow-up of 7.1 years, are presented in Table 8.

Table 8. Relative and Absolute Risk Seen in the Estrogen-Alone Substudy of WHI a
Event | Relative Risk CE vs. Placebo (95% nCI b) | CE n=5,310 | Placebo n=5,429
 |  | Absolute Risk per 10,000 Women-Years
CHD events c | 0.95 (0.78–1.16) | 54 | 57
Nonfatal MIc | 0.91 (0.73–1.14) | 40 | 43
CHD deathc | 1.01 (0.71–1.43) | 16 | 16
All strokesc | 1.33 (1.05–1.68) | 45 | 33
Ischemic strokec | 1.55 (1.19–2.01) | 38 | 25
Deep vein thrombosisc,d | 1.47 (1.06–2.06) | 23 | 15
Pulmonary embolismc | 1.37 (0.90–2.07) | 14 | 10
Invasive breast cancerc | 0.80 (0.62–1.04) | 28 | 34
Colorectal cancere | 1.08 (0.75–1.55) | 17 | 16
Hip fracturec | 0.65 (0.45–0.94) | 12 | 19
Vertebral fracturesc,d | 0.64 (0.44–0.93) | 11 | 18
Lower arm/wrist fracturesc,d | 0.58 (0.47–0.72) | 35 | 59
Total fracturesc,d | 0.71 (0.64–0.80) | 144 | 197
Death due to other causese,f | 1.08 (0.88–1.32) | 53 | 50
Overall mortalityc,d | 1.04 (0.88–1.22) | 79 | 75
Global Indexg | 1.02 (0.92–1.13) | 206 | 201
aAdapted from numerous WHI publications. WHI publications can be viewed at www.nhlbi.nih.gov/whi.
bNominal CI unadjusted for multiple looks and multiple comparisons.
cResults are based on centrally adjudicated data for an average follow-up of 7.1 years.
dNot included in “global index”.
eResults are based on an average follow-up of 6.8 years.
fAll deaths, except from breast or colorectal cancer, definite or probable CHD, PE or cerebrovascular disease.
gA subset of the events was combined in a “global index”, defined as the earliest occurrence of CHD events, invasive breast cancer, stroke, pulmonary embolism, colorectal cancer, hip fracture, or death due to other causes.

For those outcomes included in the WHI “global index” that reached statistical significance, the absolute excess risk per 10,000 women-years in the group treated with CE-alone was 12 more strokes, while the absolute risk reduction per 10,000 women-years was 7 fewer hip fractures.^9 The absolute excess risk of events included in the “global index” was a nonsignificant 5 events per 10,000 women-years. There was no difference between the groups in terms of all-cause mortality.

No overall difference for primary CHD events (nonfatal MI, silent MI and CHD death) and invasive breast cancer incidence in women receiving CE-alone compared with placebo was reported in final centrally adjudicated results from the estrogen-alone substudy, after an average follow-up of 7.1 years (see Table 8).

Centrally adjudicated results for stroke events from the estrogen-alone substudy, after an average follow-up of 7.1 years, reported no significant difference in distribution of stroke subtype or severity, including fatal strokes, in women receiving CE-alone compared to placebo. Estrogen-alone increased the risk for ischemic stroke, and this excess was present in all subgroups of women examined.^10 (see Table 8).

Timing of the initiation of estrogen therapy relative to the start of menopause may affect the overall risk benefit profile. The WHI estrogen-alone substudy stratified by age showed in women 50 to 59 years of age, a nonsignificant trend toward reduced risk for CHD [HR 0.63 (95 percent, CI 0.36 to 1.09)] and overall mortality [HR 0.71 (95 percent CI, 0.46 to 1.11)].

Women’s Health Initiative Memory Study

The WHIMS estrogen plus progestin ancillary study of WHI enrolled 4,532 predominantly healthy postmenopausal women 65 years of age and older (47 percent were 65 to 69 years of age; 35 percent were 70 to 74 years of age; 18 percent were 75 years of age and older) to evaluate the effects of daily CE (0.625 mg) plus MPA (2.5 mg) on the incidence of probable dementia (primary outcome) compared to placebo.

After an average follow-up of 4 years, the relative risk of probable dementia for CE plus MPA versus placebo was 2.05 (95 percent CI, 1.21 to 3.48). The absolute risk of probable dementia for CE plus MPA versus placebo was 45 versus 22 cases per 10,000 women-years. Probable dementia as defined in this study included Alzheimer disease (AD), vascular dementia (VaD) and mixed type (having features of both AD and VaD). The most common classification of probable dementia in the treatment group and the placebo group was AD. Since the ancillary study was conducted in women 65 to 79 years of age, it is unknown whether these findings apply to younger postmenopausal women. (See WARNINGS, Probable Dementia and PRECAUTIONS, Geriatric Use)

The WHIMS estrogen-alone ancillary study of WHI enrolled 2,947 predominantly healthy hysterectomized postmenopausal women 65 to 79 years of age (45 percent were 65 to 69 years of age; 36 percent were 70 to 74 years of age; 19 percent were 75 years of age and older) to evaluate the effects of daily CE (0.625 mg)-alone on the incidence of probable dementia (primary outcome) compared to placebo.

After an average follow-up of 5.2 years, the relative risk of probable dementia for CE-alone versus placebo was 1.49 (95 percent CI, 0.83 to 2.66). The absolute risk of probable dementia for CE-alone versus placebo was 37 versus 25 cases per 10,000 women-years. Probable dementia as defined in this study included AD, VaD and mixed type (having features of both AD and VaD). The most common classification of probable dementia in the treatment group and the placebo group was AD. Since the ancillary study was conducted in women 65 to 79 years of age, it is unknown whether these findings apply to younger postmenopausal women. (See WARNINGS, Probable Dementia and PRECAUTIONS, Geriatric Use)

When data from the two populations were pooled as planned in the WHIMS protocol, the reported overall relative risk for probable dementia was 1.76 (95 percent CI, 1.19 to 2.60). Differences between groups became apparent in the first year of treatment. It is unknown whether these findings apply to younger postmenopausal women. (See WARNINGS, Probable Dementia and PRECAUTIONS, Geriatric Use)

INDICATIONS AND USAGE

CombiPatch is indicated in a woman with a uterus for:

- Treatment of moderate to severe vasomotor symptoms due to menopause.
- Treatment of moderate to severe symptoms of vulvar and vaginal atrophy due to menopause. When prescribing solely for the treatment of symptoms of vulvar and vaginal atrophy, topical vaginal products should be considered.
- Treatment of hypoestrogenism due to hypogonadism, castration, or primary ovarian failure.

CONTRAINDICATIONS

CombiPatch is contraindicated in women with any of the following conditions:

1. Undiagnosed abnormal genital bleeding.
2. Known, suspected, or history of breast cancer.
3. Known or suspected estrogen-dependent neoplasia.
4. Active DVT, PE, or history of these conditions.
5. Active arterial thromboembolic disease (for example, stroke and MI), or a history of these conditions.
6. Known anaphylactic reaction or angioedema or hypersensitivity with CombiPatch.
7. Known liver impairment or disease.
8. Known protein C, protein S, or antithrombin deficiency, or other known thrombophilic disorders.
9. Known or suspected pregnancy.

WARNINGS

See BOXED WARNING.

1. Cardiovascular Disorders

An increased risk of PE, DVT, stroke and MI has been reported with estrogen plus progestin therapy. An increased risk of stroke and DVT has been reported with estrogen-alone therapy. Should any of these occur or be suspected, estrogen with or without progestin therapy should be discontinued immediately.

Risk factors for arterial vascular disease (for example, hypertension, diabetes mellitus, tobacco use, hypercholesterolemia, and obesity) and/or venous thromboembolism (VTE) (for example, personal history or family history of VTE, obesity, and systemic lupus erythematosus) should be managed appropriately.

a. Stroke

In the WHI estrogen plus progestin substudy, a statistically significant increased risk of stroke was reported in women 50 to 79 years of age receiving daily CE (0.625 mg) plus MPA (2.5 mg) compared to women in the same age group receiving placebo (33 versus 25 per 10,000 women-years). (See CLINICAL STUDIES) The increase in risk was demonstrated after the first year and persisted. ^1 Should a stroke occur or be suspected, estrogen plus progestin therapy should be discontinued immediately.

In the WHI estrogen-alone substudy, a statistically significant increased risk of stroke was reported in women 50 to 79 years of age receiving daily CE (0.625 mg)-alone compared to women in the same age group receiving placebo (45 versus 33 per 10,000 women-years). (See CLINICAL STUDIES) The increase in risk was demonstrated in year 1 and persisted. Should a stroke occur or be suspected, estrogen-alone therapy should be discontinued immediately.

Subgroup analyses of women 50 to 59 years of age suggest no increased risk of stroke for those women receiving CE (0.625 mg)-alone versus those receiving placebo (18 versus 21 per 10,000 women-years). ^1

b. Coronary Heart Disease

In the WHI estrogen plus progestin substudy, there was a statistically non-significant increased risk of CHD events (defined as nonfatal MI, silent MI, or CHD death) reported in women receiving daily CE (0.625 mg) plus MPA (2.5 mg) compared to women receiving placebo (41 versus 34 per 10,000 women years). ^1 An increase in relative risk was demonstrated in year 1, and a trend toward decreasing relative risk was reported in years 2 through 5 (See CLINICAL STUDIES).

In the WHI estrogen-alone substudy, no overall effect on CHD events was reported in women receiving estrogen-alone compared to placebo. ^2 (See CLINICAL STUDIES)

Subgroup analyses of women 50 to 59 years of age suggest a statistically nonsignificant reduction in CHD events (CE [0.625 mg]-alone compared to placebo) in women less than 10 years since menopause (8 versus 16 per 10,000 women-years). ^1

In postmenopausal women with documented heart disease (n=2,763, average 66.7 years of age), in a controlled clinical trial of secondary prevention of cardiovascular disease (Heart and Estrogen/Progestin Replacement Study; HERS), treatment with daily CE (0.625 mg) plus MPA (2.5 mg) demonstrated no cardiovascular benefit. During an average follow-up of 4.1 years, treatment with CE plus MPA did not reduce the overall rate of CHD events in postmenopausal women with established CHD. There were more CHD events in the CE plus MPA-treated group than in the placebo group in year 1, but not during the subsequent years. Two thousand three hundred twenty-one (2,321) women from the original HERS trial agreed to participate in an open-label extension of HERS, HERS II. Average follow-up in HERS II was an additional 2.7 years, for a total of 6.8 years overall. Rates of CHD events were comparable among women in the CE plus MPA group and the placebo group in the HERS, the HERS II, and overall.

c. Venous Thromboembolism

In the WHI estrogen plus progestin substudy, a statistically significant 2-fold greater rate of VTE (DVT and PE) was reported in women receiving daily CE (0.625 mg) plus MPA (2.5 mg) compared to placebo (35 versus 17 per 10,000 women-years). Statistically significant increases in risk for both DVT (26 versus 13 per 10,000 women-years) and PE (18 versus 8 per 10,000 women years) were also demonstrated. The increase in VTE risk was demonstrated during the first year and persisted. ^3 (See CLINICAL STUDIES) Should a VTE occur or be suspected, estrogen plus progestin therapy should be discontinued immediately.

In the WHI estrogen-alone substudy, the risk of VTE was reported to be increased for women receiving daily CE (0.625 mg)-alone compared to women receiving placebo (30 versus 22 per 10,000 women-years), although only the increased risk of DVT reached statistical significance (23 versus 15 per 10,000 women years). The increase in VTE risk was demonstrated during the first 2 years. ^4 (See CLINICAL STUDIES) Should a VTE occur or be suspected, estrogen-alone therapy should be discontinued immediately.

If feasible, estrogens should be discontinued at least 4 to 6 weeks before surgery of the type associated with an increased risk of thromboembolism, or during periods of prolonged immobilization.

2. Malignant Neoplasms

a. Breast Cancer

The WHI substudy of daily CE (0.625 mg)-alone provided information about breast cancer in estrogen-alone users. In the WHI estrogen-alone substudy, after an average follow-up of 7.1 years, daily CE-alone was not associated with an increased risk of invasive breast cancer (relative risk [RR] 0.80)^5 [see CLINICAL STUDIES]. After a mean follow-up of 5.6 years, the WHI substudy of daily CE (0.625 mg) plus MPA (2.5 mg) reported an increased risk of invasive breast cancer in women who took daily CE plus MPA compared to placebo. In this substudy, prior use of estrogen-alone or estrogen plus progestin therapy was reported by 26 percent of the women. The relative risk of invasive breast cancer was 1.24, and the absolute risk was 41 versus 33 cases per 10,000 women-years, for CE plus MPA compared with placebo. Among women who reported prior use of hormone therapy, the relative risk of invasive breast cancer was 1.86, and the absolute risk was 46 versus 25 cases per 10,000 women-years, for CE plus MPA compared with placebo. Among women who reported no prior use of hormone therapy, the relative risk of invasive breast cancer was 1.09, and the absolute risk was 40 versus 36 cases per 10,000 women-years for CE plus MPA compared with placebo. In the same substudy, invasive breast cancers were larger, were more likely to be node positive, and were diagnosed at a more advanced stage in the CE (0.625 mg) plus MPA (2.5 mg) group compared with the placebo group. Metastatic disease was rare, with no apparent difference between the two groups. Other prognostic factors, such as histologic subtype, grade and hormone receptor status did not differ between the groups [see CLINICAL STUDIES].

Consistent with the WHI clinical trial, observational studies have also reported an increased risk of breast cancer for estrogen plus progestin therapy, and a smaller increased risk for estrogen-alone therapy, after several years of use. One large meta-analysis of prospective cohort studies reported increased risks that were dependent upon duration of use and could last up to >10 years after discontinuation of estrogen plus progestin therapy and estrogen-alone therapy. Extension of the WHI trials also demonstrated increased breast cancer risk associated with estrogen plus progestin therapy. Observational studies also suggest that the risk of breast cancer was greater, and became apparent earlier, with estrogen plus progestin therapy as compared to estrogen-alone therapy. However, these studies have not found significant variation in the risk of breast cancer among different estrogen plus progestin combinations, doses, or routes of administration.

The use of estrogen-alone and estrogen plus progestin has been reported to result in an increase in abnormal mammograms requiring further evaluation.

All women should receive yearly breast examinations by a healthcare provider and perform monthly breast self-examinations. In addition, mammography examinations should be scheduled based on patient age, risk factors, and prior mammogram results.

b. Endometrial Cancer

An increased risk of endometrial cancer has been reported with the use of unopposed estrogen therapy in a woman with a uterus. The reported endometrial cancer risk among users of unopposed estrogen is about 2 to 12 times greater than in nonusers, and appears dependent on duration of treatment and on estrogen dose. Most studies show no significant increased risk associated with the use of estrogens for less than 1 year. The greatest risk appears associated with prolonged use with increased risks of 15- to 24-fold for 5 to 10 years or more and this risk has been shown to persist for at least 8 to 15 years after estrogen therapy is discontinued.

Clinical surveillance of all women using estrogen-alone or estrogen plus progestin therapy is important. Adequate diagnostic measures, including directed or random endometrial sampling when indicated, should be undertaken to rule out malignancy in postmenopausal women with undiagnosed persistent or recurring abnormal genital bleeding. There is no evidence that the use of natural estrogens results in a different endometrial risk profile than synthetic estrogens of equivalent estrogen dose. Adding a progestin to estrogen therapy has been shown to reduce the risk of endometrial hyperplasia, which may be a precursor to endometrial cancer.

c. Ovarian Cancer

The WHI estrogen plus progestin substudy reported a statistically nonsignificant increased risk of ovarian cancer. After an average follow-up of 5.6 years, the relative risk for ovarian cancer for CE plus MPA versus placebo was 1.58 (95 percent CI 0.77 to 3.24). The absolute risk for CE plus MPA versus placebo was 4 versus 3 cases per 10,000 women-years.^7

A meta-analysis of 17 prospective and 35 retrospective epidemiology studies found that women who used hormonal therapy for menopausal symptoms had an increased risk for ovarian cancer. The primary analysis, using case-control comparisons, included 12,110 cancer cases from the 17 prospective studies. The relative risks associated with current use of hormonal therapy was 1.41 (95% confidence interval [CI] 1.32 to 1.50); there was no difference in the risk estimates by duration of the exposure (less than 5 years [median of 3 years]vs. greater than 5 years [median of 10 years] of use before the cancer diagnosis). The relative risk associated with combined current and recent use (discontinued use within 5 years before cancer diagnosis) was 1.37 (95% CI 1.27-1.48), and the elevated risk was significant for both estrogen-alone and estrogen plus progestin products. The exact duration of hormone therapy use associated with an increased risk of ovarian cancer, however, is unknown.

3. Probable Dementia

In the WHIMS estrogen plus progestin ancillary substudy of WHI, a population of 4,532 generally healthy postmenopausal women 65 to 79 years of age was randomized to daily CE (0.625 mg) plus MPA (2.5 mg) or placebo.

After an average follow-up of 4 years, 40 women in the CE plus MPA group and 21 women in the placebo group were diagnosed with probable dementia. The relative risk for CE plus MPA versus placebo was 2.05 (95 percent CI, 1.21 to 3.48). The absolute risk of probable dementia for CE plus MPA versus placebo was 45 versus 22 cases per 10,000 women-years.^8 (See CLINICAL STUDIES and PRECAUTIONS, Geriatric Use)

In the WHIMS estrogen-alone ancillary study of WHI, a population of 2,947 hysterectomized women 65 to 79 years of age was randomized to daily CE (0.625 mg)-alone or placebo. After an average follow-up of 5.2 years, 28 women in the estrogen-alone group and 19 women in the placebo group were diagnosed with probable dementia. The relative risk of probable dementia for CE-alone versus placebo was 1.49 (95 percent CI, 0.83 to 2.66). The absolute risk of probable dementia for CE-alone versus placebo was 37 versus 25 cases per 10,000 women-years.^8 (See CLINICAL STUDIES and PRECAUTIONS, Geriatric Use)

When data from the 2 populations in the WHIMS estrogen-alone and estrogen plus progestin ancillary studies were pooled as planned in the WHIMS protocol, the reported overall relative risk for probable dementia was 1.76 (95 percent CI, 1.19 to 2.60). Since both ancillary studies were conducted in women 65 to 79 years of age, it is unknown whether these findings apply to younger postmenopausal women.^8 (See PRECAUTIONS, Geriatric Use)

4. Gallbladder Disease

A 2- to 4-fold increase in the risk of gallbladder disease requiring surgery in postmenopausal women receiving estrogens has been reported.

5. Hypercalcemia

Estrogen administration may lead to severe hypercalcemia in patients with breast cancer and bone metastases. If hypercalcemia occurs, use of the drug should be stopped and appropriate measures taken to reduce the serum calcium level.

6. Visual Abnormalities

Retinal vascular thrombosis has been reported in women receiving estrogens. Discontinue medication pending examination if there is sudden partial or complete loss of vision, or a sudden onset of proptosis, diplopia, or migraine. If examination reveals papilledema or retinal vascular lesions, estrogens should be permanently discontinued.

7. Angioedema

Angioedema involving eye/eyelid, face, larynx, pharynx, tongue and extremity (hands, legs, ankles, and fingers) with or without urticaria requiring medical intervention has occurred in the postmarketing experience of using CombiPatch. If angioedema involves the tongue, glottis, or larynx, airway obstruction may occur. Women who develop angioedema anytime during the course of treatment with CombiPatch should not receive it again. Exogenous estrogens may exacerbate symptoms of angioedema in women with hereditary angioedema.

8. Severe Anaphylactic/Anaphylactoid Reactions

Cases of anaphylactic/anaphylactoid reactions, which developed anytime during the course of CombiPatch treatment and required emergency medical management, have been reported in the postmarketing setting. Involvement of skin (hives, pruritus, swollen lips-tongue-face) and either respiratory tract (respiratory compromise) or gastrointestinal tract (abdominal pain, vomiting) has been noted.

PRECAUTIONS

A. General

1. Addition of a Progestin when a Woman has not had a Hysterectomy

Studies of the addition of a progestin for 10 or more days of a cycle of estrogen administration, or daily with estrogen in a continuous regimen, have reported a lowered incidence of endometrial hyperplasia than would be induced by estrogen treatment alone. Endometrial hyperplasia may be a precursor to endometrial cancer.

There are, however, possible risks that may be associated with the use of progestins with estrogens compared to estrogen-alone regimens. These include an increased risk of breast cancer.

2. Elevated Blood Pressure

In a small number of case reports, substantial increases in blood pressure have been attributed to idiosyncratic reactions to estrogens. In a large, randomized, placebo-controlled clinical trial, a generalized effect of estrogen therapy on blood pressure was not seen.

3. Hypertriglyceridemia

In women with preexisting hypertriglyceridemia, estrogen therapy may be associated with elevations of plasma triglycerides leading to pancreatitis. Consider discontinuation of treatment if pancreatitis occurs.

4. Hepatic Impairment and/or Past History of Cholestatic Jaundice

Although transdermally administered estrogen therapy avoids first-pass hepatic metabolism, estrogens may be poorly metabolized in women with impaired liver function. For women with a history of cholestatic jaundice associated with past estrogen use or with pregnancy, caution should be exercised and in the case of recurrence, medication should be discontinued.

5. Hypothyroidism

Estrogen administration leads to increased thyroid-binding globulin (TBG) levels. Women with normal thyroid function can compensate for the increased TBG by making more thyroid hormone, thus maintaining free T4 and T3 serum concentrations in the normal range. Women dependent on thyroid hormone replacement therapy who are also receiving estrogens may require increased doses of their thyroid replacement therapy. These women should have their thyroid function monitored in order to maintain their free thyroid hormone levels in an acceptable range.

6. Fluid Retention

Estrogens plus progestins may cause some degree of fluid retention. Women with conditions which might be influenced by this factor, such as cardiac or renal impairment warrant careful observation when estrogens plus progestins are prescribed.

7. Hypocalcemia

Estrogen therapy should be used with caution in women with hypoparathyroidism as estrogen-induced hypocalcemia may occur.

8. Exacerbation of Endometriosis

A few cases of malignant transformation of residual endometrial implants have been reported in women treated post-hysterectomy with estrogen-alone therapy. For women known to have residual endometriosis post-hysterectomy, the addition of progestin should be considered.

9. Exacerbation of Other Conditions

Estrogen therapy may cause an exacerbation of asthma, diabetes mellitus, epilepsy, migraine or porphyria, systemic lupus erythematosus, and hepatic hemangiomas and should be used with caution in women with these conditions.

B. Patient Information

Physicians are advised to discuss the content of the PATIENT INFORMATION leaflet and INSTRUCTIONS FOR USE with patients for whom they prescribe CombiPatch.

C. Laboratory Tests

Serum FSH and estradiol levels have not been shown to be useful in the management of moderate to severe vasomotor symptoms and moderate to severe symptoms of vulvar and vaginal atrophy.

Laboratory parameters may be useful in guiding dosage for the treatment of hypoestrogenism due to hypogonadism, castration and primary ovarian failure.

D. Drug-Laboratory Test Interactions

1. Accelerated prothrombin time, partial thromboplastin time, and platelet aggregation time; increased platelet count; increased factors II, VII antigen, VIII antigen, VIII coagulant activity, IX, X, XII, VII-X complex, II-VII-X complex; and beta-thromboglobulin; decreased levels of anti-factor Xa and antithrombin III; decreased antithrombin III activity; increased levels of fibrinogen and fibrinogen activity; increased plasminogen antigen and activity.

2. Increased TBG leading to increased circulating total thyroid hormone, as measured by protein-bound iodine (PBI), T4 levels (by column or by radioimmunoassay) or T3 levels by radioimmunoassay. T 3 resin uptake is decreased, reflecting the elevated TBG. Free T4 and free T3 concentrations are unaltered. Women on thyroid replacement therapy may require higher doses of thyroid hormone.

3. Other binding proteins may be elevated in serum (i.e., corticosteroid binding globulin [CBG], SHBG), leading to increased circulating corticosteroids and sex steroids, respectively. Free hormone concentrations, such as testosterone and estradiol, may be decreased. Other plasma proteins may be increased (angiotensinogen/renin substrate, alpha-1-antitrypsin, ceruloplasmin).

4. Increased plasma high density lipoprotein (HDL) and HDL-2 subfraction concentrations, reduced low density lipoprotein (LDL) cholesterol concentration, increased triglycerides levels.

5. Impaired glucose tolerance.

E. Carcinogenesis, Mutagenesis, Impairment of Fertility

Long-term continuous administration of natural and synthetic estrogens in certain animal species increases the frequency of carcinomas of the breast, uterus, cervix, vagina, testis, and liver.

NETA was not mutagenic in a battery of in vitro or in vivo genetic toxicity assays.

F. Pregnancy

CombiPatch should not be used during pregnancy. (See CONTRAINDICATIONS.) There appears to be little or no increased risk of birth defects in children born to women who have used estrogens and progestins as an oral contraceptive inadvertently during early pregnancy.

G. Nursing Mothers

CombiPatch should not be used during lactation. Estrogen administration to nursing women has been shown to decrease the quantity and quality of the breast milk. Detectable amounts of estrogens and progestins have been identified in the breast milk of women receiving these drugs. Caution should be exercised when CombiPatch is administered to a nursing woman.

H. Pediatric Use

CombiPatch is not indicated in children. Clinical studies have not been conducted in the pediatric population.

I. Geriatric Use

There have not been sufficient numbers of geriatric women involved in studies utilizing CombiPatch to determine whether those over 65 years of age differ from younger subjects in their response to CombiPatch.

The Women’s Health Initiative Studies

In the WHI estrogen plus progestin substudy (daily CE [0.625 mg] plus MPA [2.5 mg] versus placebo), there was a higher relative risk of nonfatal stroke and invasive breast cancer in women greater than 65 years of age. (See CLINICAL STUDIES.)

In the WHI estrogen-alone substudy (daily CE [0.625 mg]-alone versus placebo), there was a higher relative risk of stroke in women greater than 65 years of age. (See CLINICAL STUDIES.)

The Women’s Health Initiative Memory Study

In the WHIMS ancillary studies of postmenopausal women 65 to 79 years of age, there was an increased risk of developing probable dementia in women receiving estrogen plus progestin or estrogen-alone when compared to placebo. (See CLINICAL STUDIES and WARNINGS, Probable Dementia.)

Since both ancillary studies were conducted in women 65 to 79 years of age, it is unknown whether these findings apply to younger postmenopausal women. (See CLINICAL STUDIES and WARNINGS, Probable Dementia.)

ADVERSE REACTIONS

See BOXED WARNING, WARNINGS, and PRECAUTIONS.

Because clinical trials are conducted under widely varying conditions, adverse reaction rates observed in the clinical trials of a drug cannot be directly compared to rates in the clinical trials of another drug and may not reflect the rates observed in practice.

Table 9. All Adverse Reactions Regardless of Relationship Reported at a Frequency of Greater than or Equal to 5 percent with CombiPatch
 | VASOMOTOR SYMPTOM STUDIES
 | CombiPatch 0.05/0.14 mg per day† | CombiPatch 0.05/0.25 mg per day† | Placebo
 | n=113 | n=112 | n=107
Body as a Whole | 46% | 48% | 41%
Abdominal Pain | 7% | 6% | 4%
Accidental Injury | 4% | 5% | 8%
Asthenia | 8% | 12% | 4%
Back Pain | 11% | 9% | 5%
Flu Syndrome | 9% | 5% | 7%
Headache | 18% | 20% | 20%
Pain | 6% | 4% | 9%
Digestive | 19% | 23% | 24%
Diarrhea | 4% | 5% | 7%
Dyspepsia | 1% | 5% | 5%
Flatulence | 4% | 5% | 4%
Nausea | 11% | 8% | 7%
Nervous | 16% | 28% | 28%
Depression | 3% | 5% | 9%
Insomnia | 3% | 6% | 7%
Nervousness | 3% | 5% | 1%
Respiratory | 24% | 38% | 26%
Pharyngitis | 4% | 10% | 2%
Respiratory Disorder | 7% | 12% | 7%
Rhinitis | 7% | 13% | 9%
Sinusitis | 4% | 9% | 9%
Skin and Appendages | 8% | 17% | 16%
Application Site Reaction* | 2% | 6% | 4%
Urogenital | 54% | 63% | 28%
Breast Pain | 25% | 31% | 7%
Dysmenorrhea | 20% | 21% | 5%
Leukorrhea | 5% | 5% | 3%
Menstrual Disorder | 6% | 12% | 2%
Papanicolaou Smear Suspicious | 8% | 4% | 5%
Vaginitis | 6% | 13% | 5%
†Represents milligrams of estradiol/NETA delivered daily by each system.
*Application site reactions includes localized bleeding, bruising, burning, discomfort, dryness, eczema, edema, erythema, inflammation, irritation, pain, papules, paresthesia, pruritus, rash, skin discoloration, skin pigmentation, swelling, urticaria, and vesicles.

Table 10. All Adverse Reactions Regardless of Relationship Reported at a Frequency of Greater than or Equal to 5 percent with CombiPatch
 | ENDOMETRIAL HYPERPLASIA STUDIES
 | CombiPatch 0.05/0.14 mg per day† n=325 | CombiPatch 0.05/0.25 mg per day† n=312 | Vivelle 0.05 mg per day n=318
Body as a Whole | 61% | 60% | 59%
Abdominal Pain | 12% | 14% | 16%
Accidental Injury | 10% | 11% | 8%
Asthenia | 10% | 13% | 11%
Back Pain | 15% | 14% | 13%
Flu Syndrome | 14% | 10% | 7%
Headache | 25% | 17% | 21%
Infection | 5% | 3% | 3%
Pain | 19% | 15% | 13%
Digestive | 42% | 32% | 31%
Constipation | 2% | 5% | 3%
Diarrhea | 14% | 9% | 7%
Dyspepsia | 8% | 6% | 5%
Flatulence | 7% | 5% | 6%
Nausea | 8% | 12% | 11%
Tooth Disorder | 6% | 4% | 1%
Metabolic and Nutritional Disorders | 12% | 13% | 11%
Peripheral Edema | 6% | 6% | 5%
Musculoskeletal | 17% | 17% | 15%
Arthralgia | 6% | 6% | 5%
Nervous | 33% | 30% | 28%
Depression | 8% | 9% | 8%
Dizziness | 6% | 7% | 5%
Insomnia | 8% | 6% | 4%
Nervousness | 5% | 6% | 3%
Respiratory | 45% | 43% | 40%
Bronchitis | 5% | 3% | 4%
Pharyngitis | 9% | 9% | 8%
Respiratory Disorder | 13% | 9% | 13%
Rhinitis | 19% | 22% | 17%
Sinusitis | 10% | 12% | 12%
Skin and Appendages | 38% | 37% | 31%
Acne | 4% | 5% | 4%
Application Site Reaction* | 20% | 23% | 17%
Rash | 6% | 5% | 3%
Urogenital | 71% | 79% | 74%
Breast Enlargement | 2% | 7% | 2%
Breast Pain | 34% | 48% | 40%
Dysmenorrhea | 30% | 31% | 19%
Leukorrhea | 10% | 8% | 9%
Menorrhagia | 2% | 5% | 9%
Menstrual Disorder | 17% | 19% | 14%
Vaginal Hemorrhage | 3% | 6% | 12%
Vaginitis | 9% | 13% | 13%
†Represents milligrams of estradiol/NETA delivered daily by each system.
*Application site reactions includes localized bleeding, bruising, burning, discomfort, dryness, eczema, edema, erythema, inflammation, irritation, pain, papules, paresthesia, pruritus, rash, skin discoloration, skin pigmentation, swelling, urticaria, and vesicles.

Postmarketing Experience

The following additional adverse reactions have been identified during post-approval use of CombiPatch. Because these reactions are reported voluntarily from a population of uncertain size, it is not possible to reliably estimate their frequency or establish a causal relationship to drug exposure.

Genitourinary System

Endometrial hyperplasia, endocervical polyp, uterine leiomyomata, fallopian tube cyst, uterine spasms.

Breast

Breast cancer.

Cardiovascular

Hypertension, varicose veins.

Gastrointestinal

Jaundice cholestatic, cholelithiasis, gall bladder disorder, transaminases increased.

Skin

Skin discoloration.

Central Nervous System

Affect lability, libido disorder, migraine, vertigo, paresthesia.

Miscellaneous

Angioedema, hypersensitivity, weight increased.

OVERDOSAGE

Overdosage of estrogen or estrogen plus progestin may cause nausea, vomiting, breast tenderness, abdominal pain, drowsiness and fatigue, and withdrawal bleeding may occur in women. Treatment of overdose consists of discontinuation of CombiPatch therapy with institution of appropriate symptomatic care.

DOSAGE AND ADMINISTRATION

Generally, when estrogen therapy is prescribed for a postmenopausal woman with a uterus, a progestin should be considered to reduce the risk of endometrial cancer. A woman without a uterus generally does not need a progestin. In some cases, however, hysterectomized women with a history of endometriosis may need a progestin. Use of estrogen-alone or in combination with a progestin, should be with the lowest effective dose and for the shortest duration consistent with treatment goals and risks for the individual woman. Postmenopausal women should be reevaluated periodically as clinically appropriate to determine whether treatment is still necessary. Adequate diagnostic measures, such as directed or random endometrial sampling, when indicated, should be undertaken to rule out malignancy in a postmenopausal woman with a uterus with undiagnosed persistent or recurring abnormal genital bleeding.

Initiation of Therapy

Patients should be started at the lowest dose. Estrogens with or without progestins should be prescribed at the lowest effective doses and for the shortest duration consistent with treatment goals and risks for the individual woman. The lowest effective dose of CombiPatch has not been determined in clinical trials.

Women not currently using continuous estrogen or combination estrogen plus progestin therapy may start therapy with CombiPatch at any time. However, women currently using continuous estrogen or combination estrogen plus progestin therapy should complete the current cycle of therapy, before initiating CombiPatch therapy.

Women often experience withdrawal bleeding at the completion of the cycle. The first day of this bleeding would be an appropriate time to begin CombiPatch therapy.

Therapeutic Regimens

Combination estrogen plus progestin regimens are indicated for women with an intact uterus. Two CombiPatch (estradiol/NETA) transdermal delivery systems are available: 0.05 mg estradiol with 0.14 mg NETA per day (9 cm^2) and 0.05 mg estradiol with 0.25 mg NETA per day (16 cm^2). The lowest effective dose should be used. For all regimens, women should be reevaluated at 3- to 6-month intervals to determine if changes in hormone therapy or if continued hormone therapy is appropriate.

Continuous Combined Regimen

CombiPatch 0.05 mg estradiol/0.14 mg NETA per day (9 cm^2) matrix transdermal system is used for continuous uninterrupted treatment applied twice weekly on the lower abdomen. A new system should be applied to the skin every 3 to 4 days (twice weekly) during a 28-day cycle.

Additionally, a dose of 0.05 mg estradiol/0.25 mg NETA (16 cm^2 system) is available if a greater progestin dose is desired. Irregular bleeding may occur particularly in the first six months, but generally decreases with time, and often to an amenorrheic state.

Continuous Sequential Regimen

CombiPatch can be applied as a sequential regimen in combination with an estradiol-only transdermal delivery system.

In this treatment regimen, a 0.05 mg per day (nominal delivery rate) estradiol transdermal system (Vivelle-Dot®) is worn for the first 14 days of a 28-day cycle, replacing the system every 3 to 4 days (twice weekly) according to product directions.

For the remaining 14 days of the 28-day cycle, CombiPatch 0.05 mg estradiol/0.14 mg NETA per day (9 cm^2) transdermal system should be worn continuously on the lower abdomen. The CombiPatch system should be replaced every 3 to 4 days (twice weekly) during this 14-day period in the 28-day cycle.

Additionally, a dose of 0.05 mg estradiol/0.25 mg NETA (16 cm^2 system) is available if a greater progestin dose is desired. Women should be advised that monthly withdrawal bleeding often occurs.

Application of the System

Site Selection

CombiPatch should be placed on a smooth (fold-free), clean, dry area of the skin on the lower abdomen. CombiPatch should not be applied to or near the breasts. The area selected should not be oily (which can impair adherence of the system), damaged, or irritated. The waistline should be avoided, since tight clothing may rub the system off or modify drug delivery. The sites of application must be rotated, with an interval of at least one week allowed between applications to the same site.

Application

After opening the pouch, remove 1 side of the protective liner, taking care not to touch the adhesive part of the transdermal delivery system with the fingers. Immediately apply the transdermal delivery system to a smooth (fold-free) area of skin on the lower abdomen. Remove the second side of the protective liner and press the system firmly in place with the hand for at least 10 seconds, making sure there is good contact, especially around the edges.

Care should be taken that the system does not become dislodged during bathing and other activities. If a system should fall off, the same system may be reapplied to another area of the lower abdomen. If necessary, a new transdermal system may be applied, in which case, the original treatment schedule should be continued. Only 1 system should be worn at any 1 time during the 3- to 4-day dosing interval.

Once in place, the transdermal system should not be exposed to the sun for prolonged periods of time.

Removal of the System

Removal of the system should be done carefully and slowly to avoid irritation of the skin. Should any adhesive remain on the skin after removal of the system, allow the area to dry for 15 minutes. Then gently rub the area with an oil-based cream or lotion to remove the adhesive residue.

HOW SUPPLIED

CombiPatch estradiol/NETA transdermal delivery system is available in:

System | Nominal Delivery Rate *
Size | Estradiol/NETA | Presentation | NDC | Markings
9 cm ^2 | 0.05/0.14 mg per day | 8 systems per carton | 68968-0514-8 | CombiPatch 0.05/0.14 mg per day
16 cm ^2 | 0.05/0.25 mg per day | 8 systems per carton | 68968-0525-8 | CombiPatch 0.05/0.25 mg per day
*Nominal delivery rate described. See DESCRIPTION for more details regarding drug delivery.

Storage Conditions

Store CombiPatch in the refrigerator at 36℉ to 46℉ (2℃ to 8℃).

Store the systems in the sealed foil pouch.

Do not store the system in areas where extreme temperatures can occur.

Keep this and all medicines out of the reach of children.

Vivelle® is a registered trademark of Novartis Corporation. & Vivelle-Dot ® is a registered trademark of Novartis AG.

REFERENCES

1. Rossouw JE, et al. Postmenopausal Hormone Therapy and Risk of Cardiovascular Disease by Age and Years Since Menopause. JAMA. 2007;297:1465-1477.
2. Hsia J, et al. Conjugated Equine Estrogens and Coronary Heart Disease. Arch Int Med. 2006;166:357-365.
3. Cushman M, et al. Estrogen Plus Progestin and Risk of Venous Thrombosis. JAMA. 2004;292:1573-1580.
4. Curb JD, et al. Venous Thrombosis and Conjugated Equine Estrogen in Women Without a Uterus. Arch Int Med. 2006;166:772-780.
5. Chlebowski RT, et al. Influence of Estrogen Plus Progestin on Breast Cancer and Mammography in Healthy Postmenopausal Women. JAMA. 2003;289:3234-3253.
6. Stefanick ML, et al. Effects of Conjugated Equine Estrogens on Breast Cancer and Mammography Screening in Postmenopausal Women With Hysterectomy. JAMA. 2006;295:1647-1657.
7. Anderson GL, et al. Effects of Estrogen Plus Progestin on Gynecologic Cancers and Associated Diagnostic Procedures. JAMA. 2003;290:1739-1748.
8. Shumaker SA, et al. Conjugated Equine Estrogens and Incidence of Probable Dementia and Mild Cognitive Impairment in Postmenopausal Women. JAMA. 2004;291:2947-2958.
9. Jackson RD, et al. Effects of Conjugated Equine Estrogen on Risk of Fractures and BMD in Postmenopausal Women With Hysterectomy: Results From the Women's Health Initiative Randomized Trial. J Bone Miner Res. 2006;21:817-828.
10. Hendrix SL, et al. Effects of Conjugated Equine Estrogen on Stroke in the Women's Health Initiative. Circulation. 2006;113:2425-2434.

CombiPatch® is a registered trademark of Noven Pharmaceuticals, Inc.

Manufactured by:
Noven Pharmaceuticals Inc.
Miami, FL 33186

Distributed by:
Noven Therapeutics, LLC
Miami, FL 33186

© 2024 Noven Pharmaceuticals, Inc.

For more information call 1-800-455-8070 or visit www.combipatch.com.

102538-5

Patient Information

CombiPatch
(käm-bē `pach)
(estradiol/norethindrone acetate transdermal system)

Read this Patient Information before you start using CombiPatch and each time you get a refill. There may be new information. This information does not take the place of talking to your healthcare provider about your menopausal symptoms or your treatment.

What is the most important information I should know about CombiPatch (a combination of estrogen and progestin hormones)?

- Do not use estrogens with progestins to prevent heart disease, heart attacks, strokes, or dementia (decline of brain function).
- Using estrogens with progestins may increase your chances of getting heart attacks, strokes, breast cancer, or blood clots.
- Using estrogens with progestins may increase your chance of getting dementia, based on a study of women 65 years of age or older.
- Do not use estrogen-alone to prevent heart disease, heart attacks, strokes or dementia.
- Using estrogen-alone may increase your chances of getting cancer of the uterus (womb).
- Using estrogen-alone may increase your chance of getting stroke or blood clots.
- Using estrogen-alone may increase your chance of getting dementia, based on a study of women 65 years of age or older.
- You and your healthcare provider should talk regularly about whether you still need treatment with CombiPatch.

What is CombiPatch?

CombiPatch is a prescription medicine patch (Transdermal System) that contains 2 kinds of hormones, estrogen and progestin.

What is CombiPatch used for?

CombiPatch is used after menopause to:

- Reduce moderate to severe hot flashes
  Estrogens are hormones made by a woman’s ovaries. The ovaries normally stop making estrogens when a woman is between 45 and 55 years old. This drop in body estrogen levels causes the “change of life” or menopause (the end of monthly menstrual periods). Sometimes, both ovaries are removed during an operation before natural menopause takes place. The sudden drop in estrogen levels causes “surgical menopause.” When estrogen levels begin dropping, some women get very uncomfortable symptoms, such as feelings of warmth in the face, neck, and chest or sudden strong feelings of heat and sweating (“hot flashes” or “hot flushes”). In some women, the symptoms are mild, and they will not need to use estrogens. In other women, symptoms can be more severe.
- Treat moderate to severe menopausal changes in and around your vagina
  You and your healthcare provider should talk regularly about whether you still need treatment with CombiPatch to control these problems. If you use CombiPatch only to treat menopausal changes in and around your vagina, talk with your healthcare provider about whether a topical vaginal product would be better for you.
- Treat certain conditions in women before menopause if their ovaries do not make enough estrogens naturally.
  You and your healthcare provider should talk regularly about whether you still need treatment with CombiPatch.

Who should not use CombiPatch?

Do not use CombiPatch if you have had your uterus (womb) removed (hysterectomy).

CombiPatch contains a progestin to decrease the chance of getting cancer of the uterus. If you do not have a uterus, you do not need a progestin and you should not use CombiPatch.

Do not start using CombiPatch if you:

- have unusual vaginal bleeding
  Vaginal bleeding after menopause may be a warning sign of cancer of the uterus (womb). Your healthcare provider should check any unusual vaginal bleeding to find out the cause.
- currently have or have had certain cancers
  Estrogens may increase the chance of getting certain types of cancers, including cancer of the breast or uterus. If you have or have had cancer, talk with your health care provider about whether you should use CombiPatch.
- had a stroke or heart attack
- currently have or have had blood clots
- currently have or have had liver problems
- have been diagnosed with a bleeding disorder
- are allergic to CombiPatch or any of its ingredients
  See the list of ingredients in CombiPatch at the end of this leaflet.
- think you may be pregnant
  CombiPatch is not for pregnant women. If you think you may be pregnant, you should have a pregnancy test and know the results. Do not use CombiPatch if the test result is positive and talk to your healthcare provider.

What should I tell my healthcare provider before I use CombiPatch?

Before you use CombiPatch, tell your healthcare provider if you:

- have any unusual vaginal bleeding
  Vaginal bleeding after menopause may be a warning sign of cancer of the uterus (womb). Your healthcare provider should check any unusual vaginal bleeding to find out the cause.
- have any other medical conditions
- Your healthcare provider may need to check you more carefully if you have certain conditions such as asthma (wheezing), epilepsy (seizures), diabetes, migraine, endometriosis, lupus, angioedema (swelling of face and tongue), or problems with your heart, liver, thyroid, kidneys, or have high calcium levels in your blood.
- are going to have surgery or will be on bed rest
  Your healthcare provider will let you know if you need to stop using CombiPatch.
- are breastfeeding
  The hormones in CombiPatch can pass into your breast milk.

Tell your healthcare provider about all the medicines you take, including prescription and nonprescription medicines, vitamins, and herbal supplements. Some medicines may affect how CombiPatch works. CombiPatch may also affect how other medicines work. Keep a list of your medicines and show it to your healthcare provider and pharmacist when you get new medicine.

How should I use CombiPatch?

- For detailed instructions, see the step-by-step instructions for using CombiPatch at the end of this Patient Information.
- Use CombiPatch exactly as your healthcare provider tells you to use it.
- CombiPatch is for skin use only.
- Change your CombiPatch 2 times each week or every 3 to 4 days.
- Apply your CombiPatch to a clean, dry area on your lower abdomen. This area must be clean, dry, and free of powder, oil or lotion for your CombiPatch to stick to your skin.
- Apply your CombiPatch to a different area of your lower abdomen each time. Do not use the same application site 2 times in the same week.
- Do not apply CombiPatch to or near your breasts.
- If you forget to apply a new CombiPatch, you should apply a new CombiPatch as soon as possible.
- Once in place, the transdermal system should not be exposed to the sun for prolonged periods of time.
- You and your healthcare provider should talk regularly (every 3 to 6 months) about your dose and whether you still need treatment with CombiPatch.

How do I change CombiPatch?

- When changing CombiPatch, slowly peel away the used CombiPatch from your skin.
- After you remove CombiPatch, you may have a small amount of stickiness (adhesive) left on your skin. If you have any adhesive left on your skin after you remove CombiPatch, allow the area to dry for 15 minutes. Gently rub the sticky area of your skin with oil or lotion to remove the adhesive.
- The new CombiPatch must be applied to a different area of your lower abdomen. This area must be clean, dry, cool and free of powder, oil or lotion. The same site should not be used again for at least 1 week after removal of CombiPatch.

What are the possible side effects of CombiPatch?

Side effects are grouped by how serious they are and how often they happen when you are treated.

Serious, but less common side effects include:

- heart attack
- stroke
- blood clots
- dementia
- breast cancer
- cancer of the lining of the uterus (womb)
- cancer of the ovary
- high blood pressure
- high blood sugar
- gallbladder disease
- liver problems
- changes in your thyroid hormone levels
- enlargement of benign tumors of the uterus (“fibroids”)
- depression

Call your healthcare provider right away if you get any of the following warning signs or any other unusual symptoms that concern you:

- new breast lumps
- unusual vaginal bleeding
- changes in vision or speech
- sudden new severe headaches
- severe pains in your chest or legs with or without shortness of breath, weakness and fatigue

Less serious, but common side effects include:

- headache
- breast pain
- irregular vaginal bleeding or spotting
- stomach or abdominal cramps, bloating
- nausea and vomiting
- hair loss
- fluid retention
- vaginal yeast infection
- redness or irritation at patch placement site

These are not all the possible side effects of CombiPatch. For more information, ask your healthcare provider or pharmacist. Tell your healthcare provider if you have any side effects that bother you or does not go away.

You may report side effects to Noven at 1-800-455-8070 or to FDA at 1-800-FDA-1088.

What can I do to lower my chances of getting a serious side effect with CombiPatch?

- Talk with your healthcare provider regularly about whether you should continue using CombiPatch.
- See your healthcare provider right away if you get vaginal bleeding while using CombiPatch.
- Have a pelvic exam, breast exam and mammogram (breast X-ray) every year unless your healthcare provider tells you something else.
- If members of your family have had breast cancer or if you have ever had breast lumps or an abnormal mammogram, you may need to have breast exams more often.
- If you have high blood pressure, high cholesterol (fat in the blood), diabetes, are overweight, or if you use tobacco, you may have higher chances for getting heart disease.
- Ask your healthcare provider for ways to lower your chances for getting heart disease.

How should I store and throw away used CombiPatch?

- Store CombiPatch in the refrigerator at 36℉ to 46℉ (2℃ to 8℃). Allow patch to reach room temperature before application.
- Do not store CombiPatch outside of its pouch.
- Used patches still contain estrogen and progestin. To throw away the patch, fold the sticky side of the patch together, place in a sturdy child-proof container, and place this container in the trash. Used patches should not be flushed in the toilet.

Keep CombiPatch and all medicines out of the reach of children.

General information about the safe and effective use of CombiPatch.

Medicines are sometimes prescribed for conditions that are not mentioned in patient information leaflets. Do not use CombiPatch for conditions for which it was not prescribed. Do not give CombiPatch to other people, even if they have the same symptoms you have. It may harm them.

This leaflet provides a summary of the most important information about CombiPatch. If you would like more information, talk with your healthcare provider or pharmacist. You can ask for information about CombiPatch that is written for health professionals. You can get more information by calling 1-800-455-8070

What are the ingredients in CombiPatch?

Active Ingredients: estradiol and norethindrone acetate

Inactive Ingredients: acrylic adhesive, silicone adhesive, oleic acid NF, povidone USP, dipropylene glycol, polyester release protective liner

102538-5

Instructions for Use

CombiPatch
(käm-bē `pach)
(estradiol/norethindrone acetate transdermal system)

Step 1. Pick the days you will change your CombiPatch.

- You will need to change your patch every 3 to 4 days (twice weekly).

Step 2. Remove CombiPatch from the pouch.

- Tear open the protective pouch at the slit (do not use scissors) and remove the patch. See Figure A.
- The pouch should not be opened until you are ready to put the patch on.

Step 3. Remove the adhesive liner.

- Peel off one side of the protective liner. See Figure B.
- Do not touch the sticky part of the patch with your fingers. See Figure B.

Step 4. Placing the CombiPatch on your skin.

- Put the sticky side of the patch on the lower abdomen (below the panty line). See Figure C.
- Peel off the second side of the protective liner. See Figure C.
- Press the patch firmly in place with your hand for about 10 seconds. See Figure D.

Note:

- Avoid the waistline, since clothing and belts may cause the CombiPatch to be rubbed off.
- Do not apply the CombiPatch to or near your breasts.
- Only apply the CombiPatch to skin that is clean, dry, and free of any powder, oil, or lotion.
- You should not apply the CombiPatch to injured, burned, or irritated skin, or areas with skin conditions (such as birth marks, tattoos, or that is very hairy).

Step 5. Press the CombiPatch firmly onto your skin.

- Rub the edges of the CombiPatch with your fingers to make sure that it will stick to your skin. See Figure E.

Note:

- Bathing, swimming, or showering will not affect the CombiPatch.
- Once in place, the patch should not be exposed to the sun for prolonged periods of time.
- If your CombiPatch falls off reapply it. If you cannot reapply the CombiPatch, apply a new CombiPatch to another area (See Figures C, D and E) and continue to follow your original placement schedule.
- If you stop using your CombiPatch or forget to apply a new CombiPatch as scheduled you may have spotting, or bleeding, and your symptoms may come back.

Step 6. Throwing away your used CombiPatch.

- When it is time to change your CombiPatch, remove the old CombiPatch before you apply a new one.
- To throw away the patch, fold the sticky side of the patch together, place it in a sturdy child-proof container, and place this container in the trash. Used patches should not be flushed in the toilet.

This Patient Information and Instructions for Use have been approved by the U.S. Food and Drug Administration.

Manufactured by:
Noven Pharmaceuticals Inc.
Miami, FL 33186

Distributed by:
Noven Therapeutics, LLC
Miami, FL 33186

For more information call 1-800-455-8070 or visit www.combipatch.com.

© 2024 Noven Pharmaceuticals, Inc.

102538-5
02/2024

PACKAGE LABEL

PRINCIPAL DISPLAY PANEL - NDC - 68968-0514-8 CombiPatch Count - 50/140

NDC 68968-0514-8
Includes 8 Systems

See New Storage Requirements

Combipatch® 50/140

(estradiol/norethindrone acetate transdermal system)

0.05/0.14 mg per day

Noven

www.combipatch.com

Twice-Weekly Rx Only

Combipatch® 50/140

(estradiol/norethindrone acetate transdermal system)

0.05/0.14 mg per day

Twice-Weekly Rx Only

Contains 0.62 mg estradiol USP and 2.7 mg norethindrone acetate (NETA) USP to provide 0.05/0.14 mg of estradiol/NETA per day.

Inactive components: a silicone and acrylic-based multi-polymeric adhesive, povidone USP, oleic acid NF, polyolefin laminate backing, polyester release liner and dipropylene glycol.

Dosage and Administration: For transdermal use only. See package insert. Allow patch to reach room temperature before application. DO NOT STORE UNPOUCHED.

Keep out of the reach of children.

Store Combipatch® refrigerated at 36°F to 46°F (2°C to 8°C)

See side panel for lot number and expiration date. www.combipatch.com

N3 68968-0514-8 0 302391-4

Noven

PLEASE READ THIS BEFORE APPLYING PATCH.

Allow patch to reach room temperature before application.

See reverse side for patient instructions.

pull To open here

LOT/EXP GTIN 00368968051480

969864

Mfd. By: Noven Pharmaceuticals, Inc.

Miami, Florida 33186

Dist. By Noven Therapeutics, LLC

Miami, Florida 33186

PACKAGE LABEL

PRINCIPAL DISPLAY PANEL - NDC - 68968-0525-8 CombiPatch Count - 50/250

NDC 68968-0525-8

Includes 8 Systems

See New Storage Requirements

Combipatch® 50/250

(estradiol/norethindrone acetate transdermal system)

0.05/0.25 mg per day

Noven

www.combipatch.com

Twice-Weekly Rx Only

Combipatch® 50/250

(estradiol/norethindrone acetate transdermal system)

0.05/0.25 mg per day

Twice-Weekly Rx Only

Contains 0.51 mg estradiol USP and 4.8 mg norethindrone acetate (NETA) USP to provide 0.05/0.25 mg of estradiol/NETA per day.

Inactive components: a silicone and acrylic-based multi-polymeric adhesive, povidone USP, oleic acid NF, polyolefin laminate backing, polyester release liner and dipropylene glycol.

Dosage and Administration: For transdermal use only. See package insert. Allow patch to reach room temperature before application. DO NOT STORE UNPOUCHED.

Keep out of the reach of children.

Store Combipatch® refrigerated at 36°F to 46°F (2°C to 8°C)

See side panel for lot number and expiration date. www.combipatch.com

N3 68968-0525-8 0 302390-4

Noven

PLEASE READ THIS BEFORE APPLYING PATCH.

Allow patch to reach room temperature before application.

See reverse side for patient instructions.

pull To open here

LOT/EXP GTIN 00368968052586

969864

Mfd. By: Noven Pharmaceuticals, Inc.

Miami, Florida 33186

Dist. By Noven Therapeutics, LLC

Miami, Florida 33186